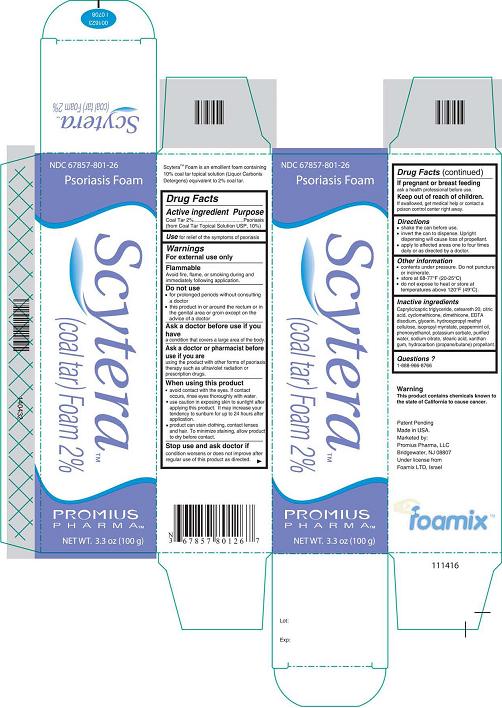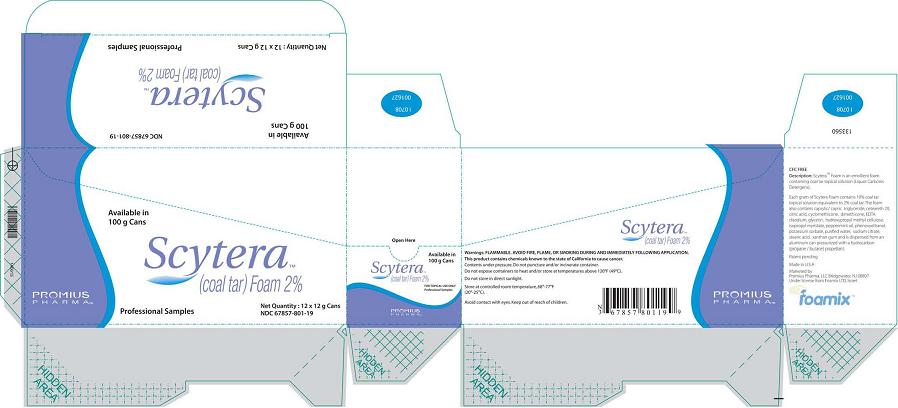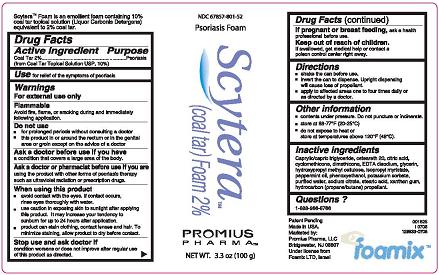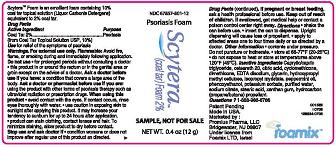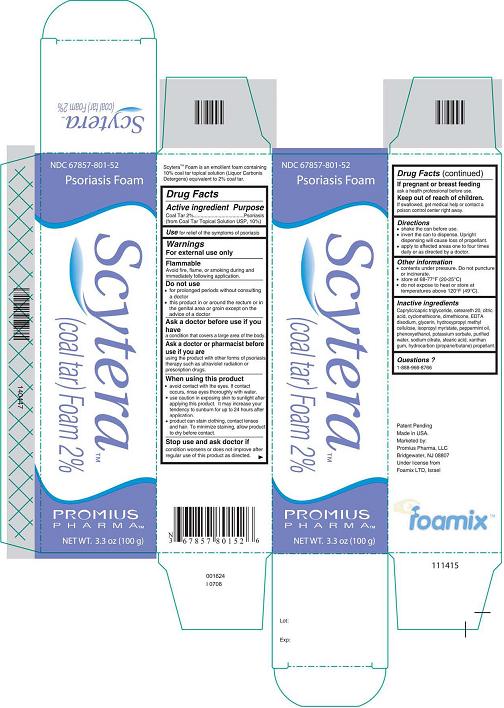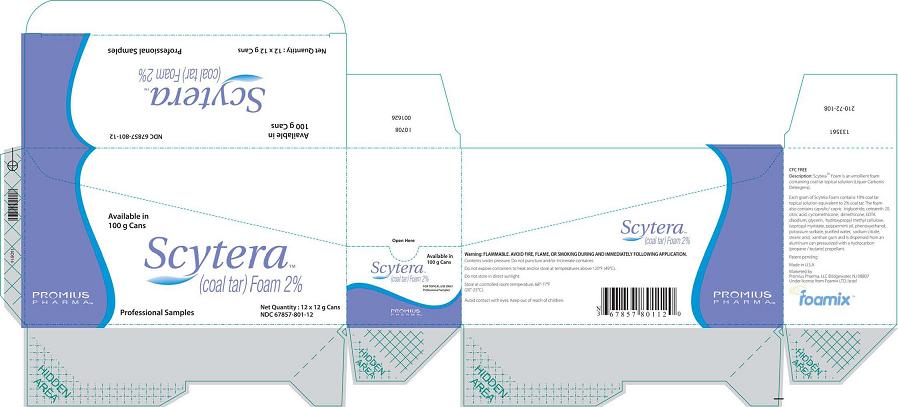 DRUG LABEL: Scytera
NDC: 63094-0801 | Form: AEROSOL, FOAM
Manufacturer: DPT Laboratories, Ltd.
Category: otc | Type: HUMAN OTC DRUG LABEL
Date: 20090818

ACTIVE INGREDIENTS: COAL TAR 20 mg/1 g
INACTIVE INGREDIENTS: GLYCERIN; HYPROMELLOSE; XANTHAN GUM; WATER; EDETATE DISODIUM; CITRIC ACID MONOHYDRATE; SODIUM CITRATE; POTASSIUM SORBATE; ISOPROPYL MYRISTATE; STEARIC ACID; PHENOXYETHANOL; PEPPERMINT OIL

DESCRIPTION

Scytera™ Foam is an emollient foam containing 10% coal tar topical solution (Liquor Carbonis Detergens) equivalent to 2% coal tar.

Active Ingredient - Purpose

Active ingredient: Coal Tar 2% (from Coal Tar Topical Solution USP, 10%)
Purpose: Psoriasis

Use

For relief of the symptoms of psoriasis.

Warnings

For external use only.
Flammable
Avoid fire, flame, or smoking during and immediately following application.

Do not use

- for prolonged periods without consulting a doctor
- this product in or around the rectum or in the genital area or groin except on the advice of a doctor

Ask a doctor before use if you have

a condition that covers a large area of your body.

Ask a doctor or pharmacist before use if you are

using the product with other forms of psoriasis therapy such as ultraviolet radiation or prescription drugs.

When using this product

- avoid contact with the eyes. If contact occurs, rinse eyes thoroughly with water.
- use caution in exposing skin to sunlight after applying this product. It may increase your tendency to sunburn for up to 24 hours after application.
- product can stain clothing, contact lenses, and hair. To minimize staining, allow product to dry before contact.

Stop use and ask doctor if

condition worsens or does not improve after regular use of this product as directed.

If pregnant or breastfeeding

ask a health professional before use.

Keep out of reach of children.

If swallowed, get medical help or contact a poison control center right away.

Directions

- shake the can well before use.
- invert the can to dispense. Upright dispensing will cause loss of propellant.
- apply to affected areas one to four times daily or as directed by a doctor.

Other information

- contents under pressure. Do not puncture or incinerate.
- store at 68°F to 77°F (20°C to 25°C)
- do not expose to heat or store at temperatures above 120°F (49°C)

Inactive Ingredients

Caprylic/capric triglyceride, ceteareth 20, citric acid, cyclomethicone, dimethicone, EDTA disodium, glycerin, hydroxypropyl methyl cellulose, isopropyl myristate, peppermint oil, phenoxyethanol, potassium sorbate, purified water, sodium citrate, stearic acid, xanthan gum, hydrocarbon (propane/butane) propellant.

Questions?

1-888-966-8766

Warning
This product contains chemicals known to the state of California to cause cancer.
Patent Pending
Made in USA.
Marketed by:
Promius Pharma, LLC
Bridgewater, NJ 08807
Under license from
Foamix LTD, Israel

Scytera™ (Coal Tar)Foam 2%, 100 g

Carton and Can Label
NDC 67857-801-52
Psoriasis Foam
Scytera™
(Coal Tar) Foam 2%
Promius Pharma™
NET WT. 3.3 oz (100 g)
Carton (California)
NDC 67857-801-26
Psoriasis Foam
Scytera™
(Coal Tar) Foam 2%
Promius Pharma™
NET WT. 3.3 oz (100 g)

Scytera™ (Coal Tar)Foam 2%, 12 g Sample Size

Packer (Box)
Available in 100 g Cans
Scytera™
(Coal Tar) Foam 2%
Promius Pharma™
Professional Samples
Net Quantity 12 x 12 g Cans
NDC 67857-801-12
Packer (Box) (California)
Available in 100 g Cans
Scytera™
(Coal Tar) Foam 2%
Promius Pharma™
Professional Samples
Net Quantity 12 x 12 g Cans
NDC 67857-801-19
Can Label
NDC 67857-801-12
Psoriasis Foam
Scytera™
(Coal Tar) Foam 2%
SAMPLE, NOT FOR SALE
NET WT. 0.4 oz (12 g)